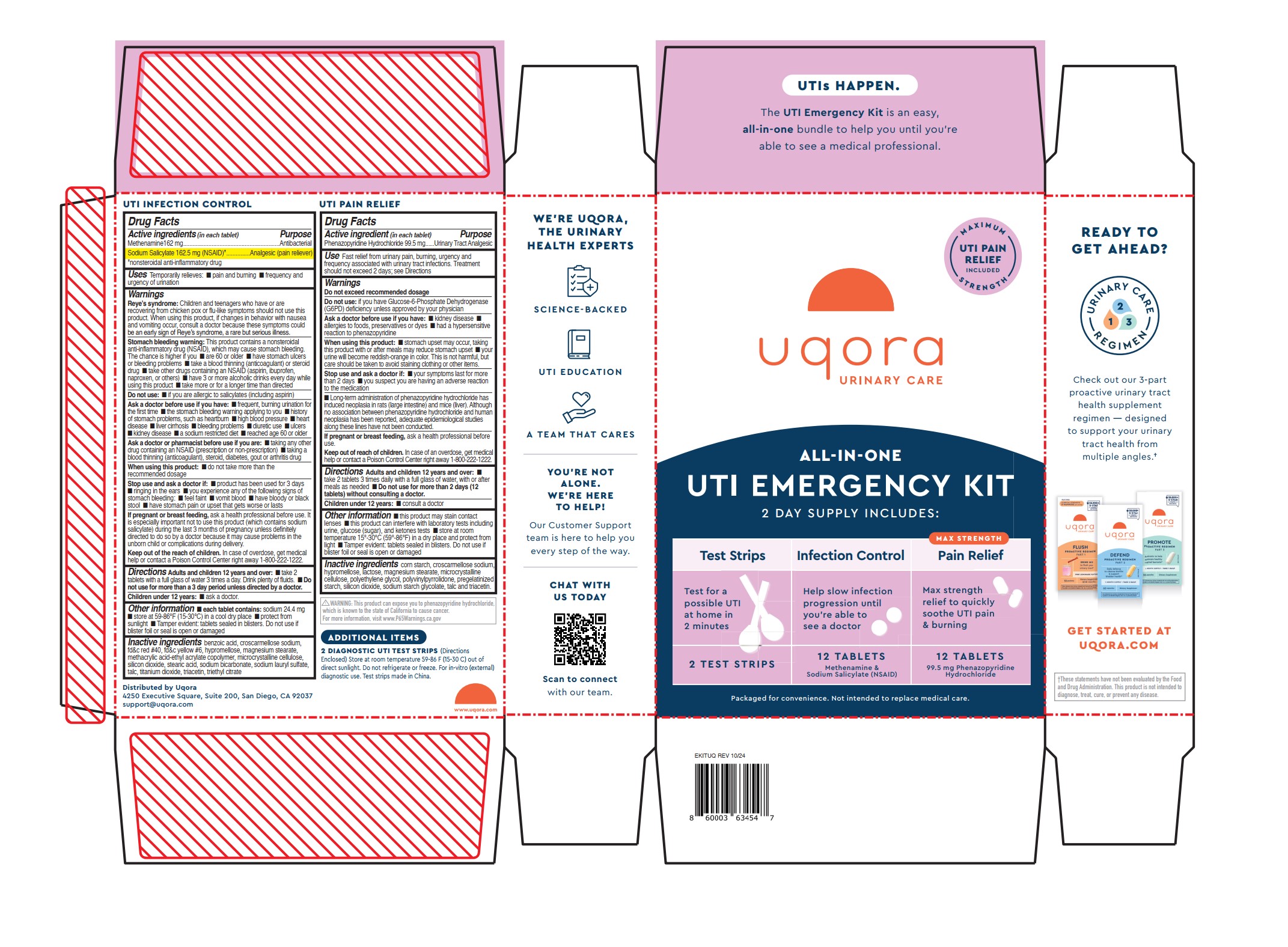 DRUG LABEL: All-In-One UTI Emergency Kit
NDC: 73712-501 | Form: KIT | Route: ORAL
Manufacturer: Bonafide Health, LLC dba Uqora
Category: otc | Type: HUMAN OTC DRUG LABEL
Date: 20251110

ACTIVE INGREDIENTS: METHENAMINE 162 mg/1 1; SODIUM SALICYLATE 162.5 mg/1 1; PHENAZOPYRIDINE HYDROCHLORIDE 99.5 mg/1 1
INACTIVE INGREDIENTS: SODIUM BICARBONATE; TRIETHYL CITRATE; FD&C YELLOW NO. 6; HYPROMELLOSES; FD&C RED NO. 40; BENZOIC ACID; CROSCARMELLOSE SODIUM; MAGNESIUM STEARATE; METHACRYLIC ACID-ETHYL ACRYLATE COPOLYMER (1:1) TYPE A; CELLULOSE, MICROCRYSTALLINE; SILICON DIOXIDE; STEARIC ACID; SODIUM LAURYL SULFATE; TALC; TITANIUM DIOXIDE; TRIACETIN; POLYETHYLENE GLYCOL, UNSPECIFIED; CELLULOSE, MICROCRYSTALLINE; HYPROMELLOSES; MAGNESIUM STEARATE; SILICON DIOXIDE; SODIUM STARCH GLYCOLATE TYPE A; CROSCARMELLOSE SODIUM; LACTOSE, UNSPECIFIED FORM; POVIDONE, UNSPECIFIED; TALC; TRIACETIN; STARCH, CORN

Uqora All-In-One UTI Emergency Kit

Drug Facts

ACTIVE INGREDIENT

Active ingredients (in each tablet) | Purpose
Methenamine 162mg | Antibacterial
Sodium Salicylate 162.5mg (NSAID)*; *nonsteroidal anti-inflammatory drug | Analgesic (pain reliever)

Active ingredient (in each tablet) | Purpose
Phenazopyridine Hydrochloride 99.5mg | Urinary Tract Analgesic

Uses

UTI Infection Control

Temporarily relieves:

- pain and burning
- frequency and urgency of urination

UTI Pain Relief

Fast relief from urinary pain, burning, urgency and frequency associated with urinary tract infections. Treatment should not exceed 2 days; see Directions.

Warnings

Reye's Syndrome (UTI Infection Control Only)

Reye’s syndrome:Children and teenagers who have or are recovering from chicken pox or flu-like symptoms should not use this
product. When using this product, if changes in behavior with nausea and vomiting occur, consult a doctor because these symptoms could be an early sign of Reye’s syndrome, a rare but serious illness.

Stomach Bleeding Warning (UTI Infection Control Only)

Stomach bleeding warning:This product contains a nonsteroidal anti-inflammatory drug (NSAID), which may cause stomach bleeding. The chance is higher if you

- are 60 or older
- have stomach ulcers or bleeding problems
- take a blood thinning (anticoagulant) or steroid drug
- take other drugs containing an NSAID (aspirin, ibuprofen, naproxen, or others)
- have 3 or more alcoholic drinks every day while using this product
- take more or for a longer time than directed

Do Not Exceed (UTI Pain Relief Only)

Do not exceed recommended dosage

Do Not Use

- If you are allergic to salicylates (including aspirin) (UTI Infection Control only)
- If you have Glucose-6-Phosphate Dehydrogenase (G6PD) deficiency unless approved by your doctor (UTI Pain Relief only)

Ask a doctor before use if you have:

- frequent, burning urination for the first time (UTI Infection Control only)
- the stomach bleeding warning applying to you (UTI Infection Control only)
- history of stomach problems, such as heartburn (UTI Infection Control only)
- high blood pressure (UTI Infection Control only)
- heart disease (UTI Infection Control only)
- liver cirrhosis (UTI Infection Control only)
- bleeding problems (UTI Infection Control only)
- diuretic use (UTI Infection Control only)
- ulcers (UTI Infection Control only)
- kidney disease
- a sodium restricted diect (UTI Infection Control only)
- reached age 60 or older (UTI Infection Control only)
- allergies to foods, preservatives or dyes (UTI Pain Relief only)
- had a hypersensitive reaction to phenazopyridine (UTI Pain Relief only)

Ask A Doctor Or Pharmacist Before Use (UTI Infection Control Only)

Ask a doctor or pharmacist before use if you are:

- taking any other drug containing an NSAID (prescription or non-prescription)
- taking a blood thinning (anticoagulant), steroid, diabetes, gout or arthritis drug

When Using This Product

- do not take more than the recommended dosage (UTI Infection Control only)
- stomach upset may occur, taking this product with or after meals may reduce stomach upset (UTI Pain Relief only)
- your urine will become reddish-orange in color. This is not harmful, but care should be taken to avoid staining clothing or other items. (UTI Pain Relief only)

Stop use and ask a doctor if:

- product has been used for 3 days (UTI Infection Control only)
- ringing in the ears (UTI Infection Control only)
- you experience any of the following signs of stomach bleeding: ■ feel faint ■ vomit blood ■ have bloody or black stool ■ have stomach pain or upset that gets worse or lasts (UTI Infection Control only)
- your symptoms last for more than 2 days (UTI Pain Relief only)
- you suspect you are having an adverse reaction to the medication (UTI Pain Relief only)

Long Term Administration (UTI Pain Relief Only)

Long-term administration of phenazopyridine hydrochloride has induced neoplasia in rats (large intestine) and mice (liver). Although
no association between phenazopyridine hydrochloride and human neoplasia has been reported, adequate epidemiological studies along these lines have not been conducted.

If Pregnant or Breast Feeding

UTI Infection Control

If pregnant or breast feeding,ask a health professional before use. It is especially important not to use this product (which contains sodium salicylate) during the last 3 months of pregnancy unless definitely directed to do so by a doctor because it may cause problems in the unborn child or complications during delivery.

UTI Pain Relief

If pregnant or breast feeding,ask a health professional before use.

Keep out of the reach of children.In case of overdose, get medical help or contact a Poison Control Center right away 1-800-222-1222

Directions

UTI Infection Control

Adults and children 12 years and over:

- take 2 tablets with a full glass of water 3 times a day. Drink plenty of fluids.
- Do not use for more than a 3 day period unless directed by a doctor.

Children under 12 years: ask a doctor.

UTI Pain Relief

Adults and children 12 years and over:

- take 2 tablets 3 times daily with a full glass of water, with or after meals as needed
- Do not use for more than 2 days (12 tablets) without consulting a doctor.

Children under 12 years:consult a doctor

Other Information

UTI Infection Control

- each tablet contains:sodium 24.4 mg
- store at 59-86°F (15-30°C) in a cool dry place
- protect from sunlight
- Tamper evident: tablets sealed in blisters. Do not use if blister foil or seal is open or damaged

UTI Pain Relief

- this product may stain contact lenses
- this product can interfere with laboratory tests including urine, glucose (sugar), and ketones tests
- store at room temperature 15°-30°C (59°-86°F) in a dry place and protect from light
- Tamper evident: tablets sealed in blisters. Do not use if blister foil or seal is open or damaged

Inactive Ingredients

UTI Infection Control

benzoic acid, croscarmellose sodium, fd&c red #40, fd&c yellow #6, hypromellose, magnesium stearate, methacrylic acid-ethyl acrylate copolymer, microcrystalline cellulose, silicon dioxide, stearic acid, sodium bicarbonate, sodium lauryl sulfate, talc, titanium dioxide, triacetin, triethyl citrate

UTI Pain Relief

corn starch, croscarmellose sodium, hypromellose, lactose, magnesium stearate, microcrystalline cellulose, polyethylene glycol, polyvinylpyrrolidone, pregelatinized starch, silicon dioxide, sodium starch glycolate, talc and triacetin.

QUESTIONS

Distributed by Uqora, Inc.

3043 4th Avenue, San Diego, CA 92103

support@uqora.com

For questions or concerns please contact (888) 313-1372

Additional Items

2 diagnostic UTI test strips(Directions Enclosed)

Other information

- store at room temperature 59-86 F (15-30 C) out of direct sunlight. Do not refrigerate or freeze
- For in-vitro (external) diagnostic use.

Principal Display Panel

uqora

Urinary Care

Maximum Strength UTI Pain Relief Included

ALL-IN-ONE

UTI EMERGENCY KIT

2 Day Supply Includes:

Test Strips

- Test for a possible UTI at home in 2 minutes
- 2 Test Strips

Infection Control

- Helps slow infection progression until you're able to see a doctor
- 12 Tablets (Methenamine & Sodium Salicylate (NSAID)

Max Strength Pain Relief

- Max strength relief to quickly soothe UTI pain & burning
- 12 Tablets (99.5mg Phenazopyridine Hydrochloride)

Packaged for convenience. Not intended to replace medical care.